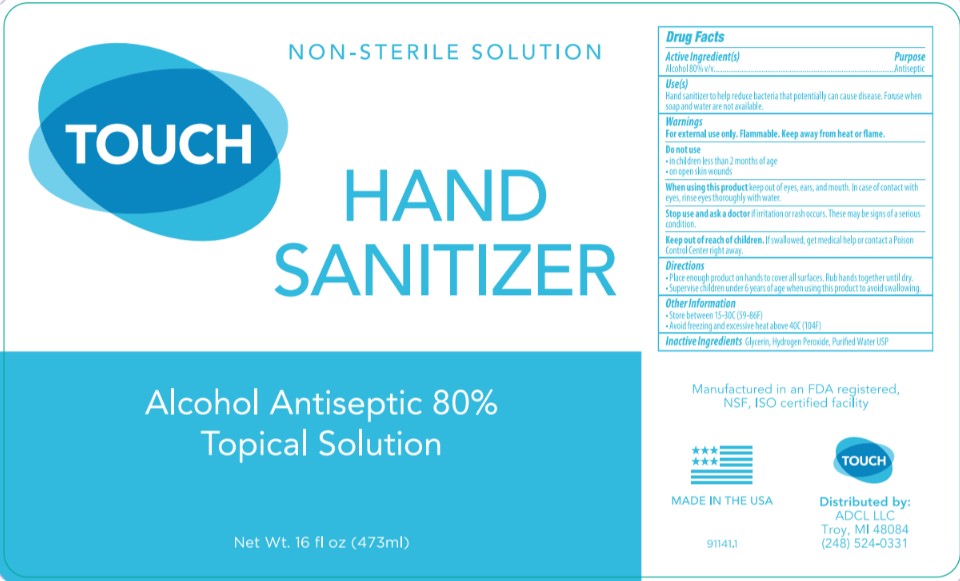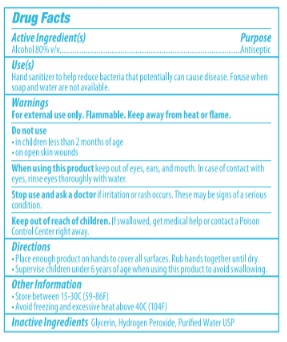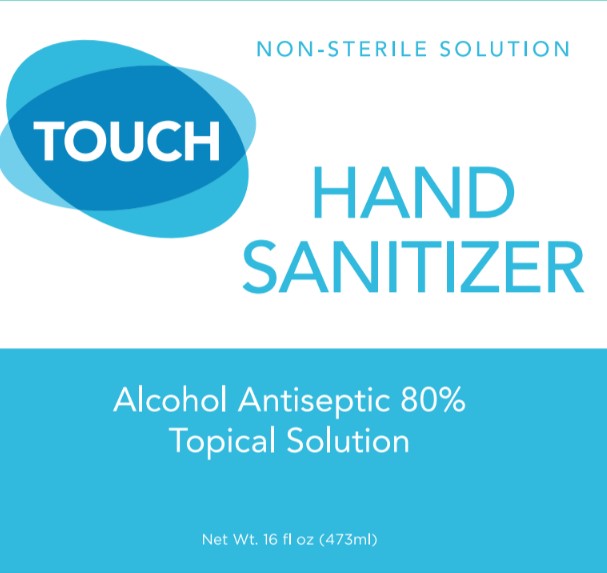 DRUG LABEL: American Dental
NDC: 73333-473 | Form: SOLUTION
Manufacturer: Nutrix International, LLC.
Category: otc | Type: HUMAN OTC DRUG LABEL
Date: 20200521

ACTIVE INGREDIENTS: ALCOHOL 0.8334 g/473 g
INACTIVE INGREDIENTS: WATER 0.14845 g/473 g; GLYCERIN 0.0145 g/473 g; HYDROGEN PEROXIDE 0.00365 g/473 g

Active Ingredient[s]

Alcohol 80%v/v

Purpose

Antiseptic

Use[s]

Hand Sanitizer to help reduce bacteria that potentially can cause disease. For use when soap and water are not available.

Warnings

For external use only. Flammable. Keep away from heat or flame.

Do not use

- On children less than 2 months of age.
- On open skin wounds

When using

When using this product keep out of eyes, ears, mouth. In case of contact with eyes, rinse thoroughly with water.

Stop use and ask a doctor

If irritation or rash occurs. These may be signs of a serious condition.

Keep out of reach of children

If swallowed, get medical help or contact a Poison Control Center right away.

Directions

- Place enough product on hands to cover all surfaces.
- Rub hands together until dry.
- Supervise children under 6 years of age when using this product to avoid swallowing.

Other Information

- Store between 15-30°C (59-86°F)
- Avoid freezing and excessive heat above 40°C (104°F)

Inactive Ingredients

Glycerin, Hydrogen Peroxide, Purified water USP

Package

Front Label